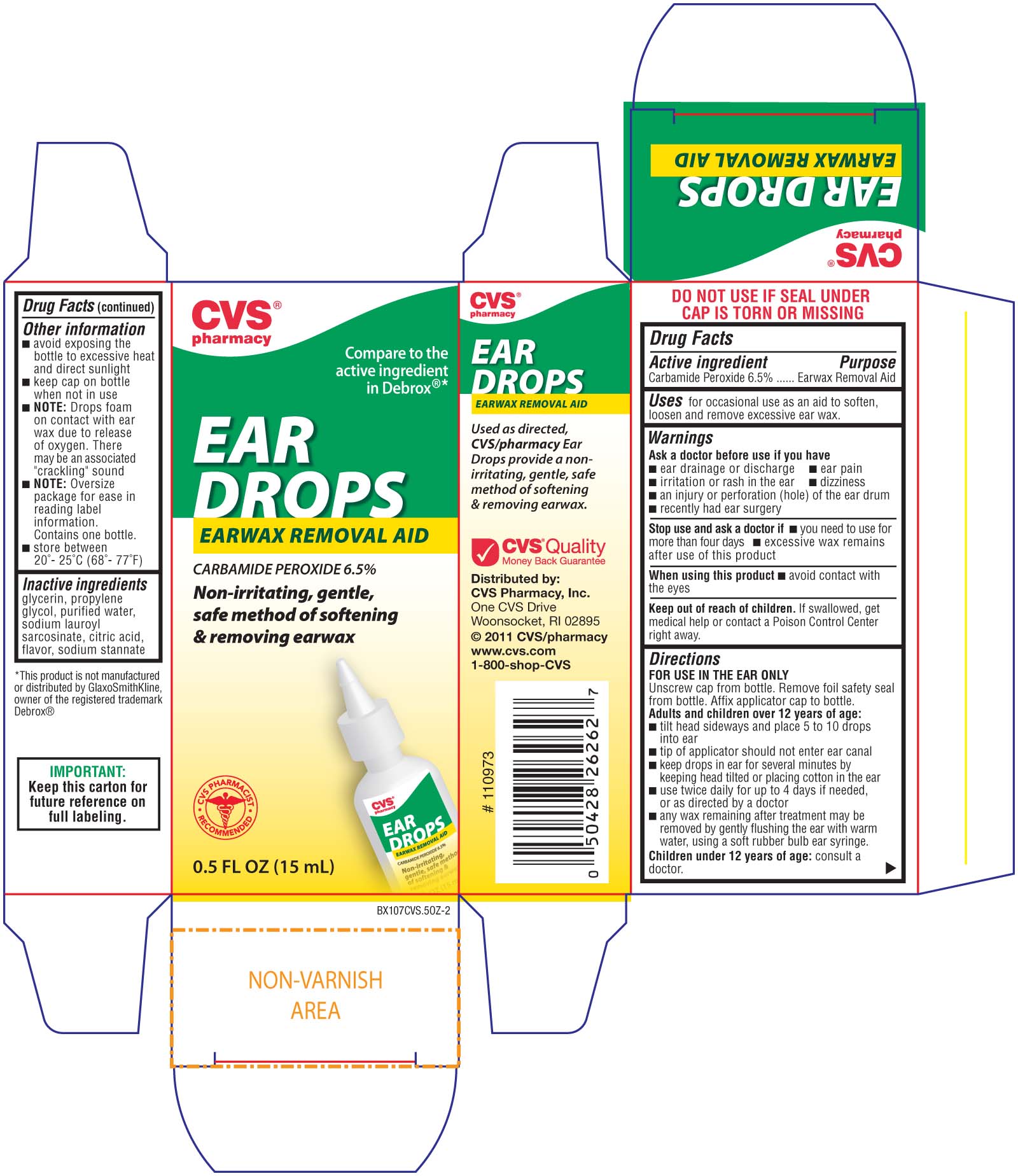 DRUG LABEL: CVS Earwax Removal Aid
NDC: 59779-257 | Form: LIQUID
Manufacturer: CVS Pharmacy
Category: otc | Type: HUMAN OTC DRUG LABEL
Date: 20110425

ACTIVE INGREDIENTS: CARBAMIDE PEROXIDE 65 mg/1 mL
INACTIVE INGREDIENTS: WATER; GLYCERIN; SODIUM LAUROYL SARCOSINATE; SODIUM STANNATE; PROPYLENE GLYCOL; CITRIC ACID MONOHYDRATE

drug facts

Active ingredient Purpose
Carbamide Peroxide 6.5%..........................Earwax Removal Aid

PURPOSE

Uses for occasional use as an aid to soften, loosen and remove excessive ear wax.

Keep out of reach of children. If swallowed, get medical help
or contact a Poison Control Center right away.

INDICATIONS AND USAGE

Uses for occasional use as an aid to soften, loosen and remove excessive ear wax.

Warnings
Ask a doctor before use if you have
- ear drainage or discharge - ear pain
- irritation or rash in the ear - dizziness
- an injury or perforation (hole) of the ear drum
- recently had ear surgery
Stop use and ask a doctor if
- you need to use for more than four days
- excessive wax remains after use of this product
When using this product - avoid contact with the eyes
Keep out of reach of children. If swallowed, get medical help or contact a Poison Control Center right away

Directions
FOR USE IN THE EAR ONLY
Unscrew cap from bottle. Remove foil safety seal from bottle. Affix applicator cap to bottle.
Adults and children over 12 years of age:
- tilt head sideways and place 5 to 10 drops into ear
- tip of applicator should not enter ear canal
- keep drops in ear for several minutes by keeping head tilted or placing cotton in the ear
- use twice daily for up to 4 days if needed, or as directed by a doctor
- any wax remaining after treatment may be removed by gently flushing the ear with warm water, using a soft rubber ear syringe.
Children under 12 years of age: consult a doctor.
Other information
- avoid exposing the bottle to excessive heat and direct sunlight
- keep cap on bottle when not in use
- Note: Drops foam on contact with ear wax due to release of oxygen. There may be an associated "cracking" sound
- Note: Oversize packaging for ease in reading label information. Contains one bottle.
- Store between 20 degrees to 25 degrees C (68 degrees to 77 degrees F)

Inactive ingredients
glycerin, propylene glycol, purified water, sodium lauroyl sarcosinate, citric acid, flavor, sodium stannate